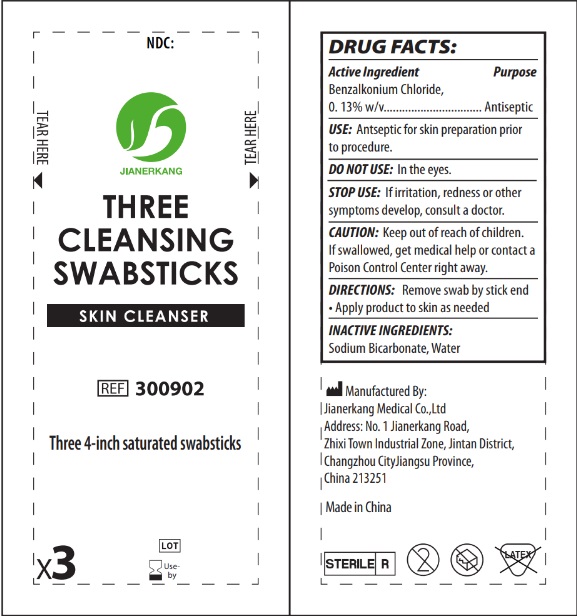 DRUG LABEL: Three Cleansing
NDC: 34645-0025 | Form: SWAB
Manufacturer: Jianerkang Medical Co., Ltd
Category: otc | Type: HUMAN OTC DRUG LABEL
Date: 20240612

ACTIVE INGREDIENTS: BENZALKONIUM CHLORIDE 1.3 mg/1 mL
INACTIVE INGREDIENTS: WATER; SODIUM BICARBONATE

Three Cleansing Swabsticks

Active ingredient

Benzalkonium Chloride, 0.13% w/v

Purpose

Antiseptic

Use

Antiseptic for skin preparation prior to procedure.

WARNINGS

DO NOT USE:

In the eyes.

STOP USE:

If irritation, redness or other symptoms develop, consult a doctor.

CAUTION:

Keep out of reach of children. If swallowed, get medical help or contact a Poison Control Center right away.

Directions

Remove swab by stick end

- Apply product to skin as needed

Inactive ingredients

Sodium Bicarbonate, water